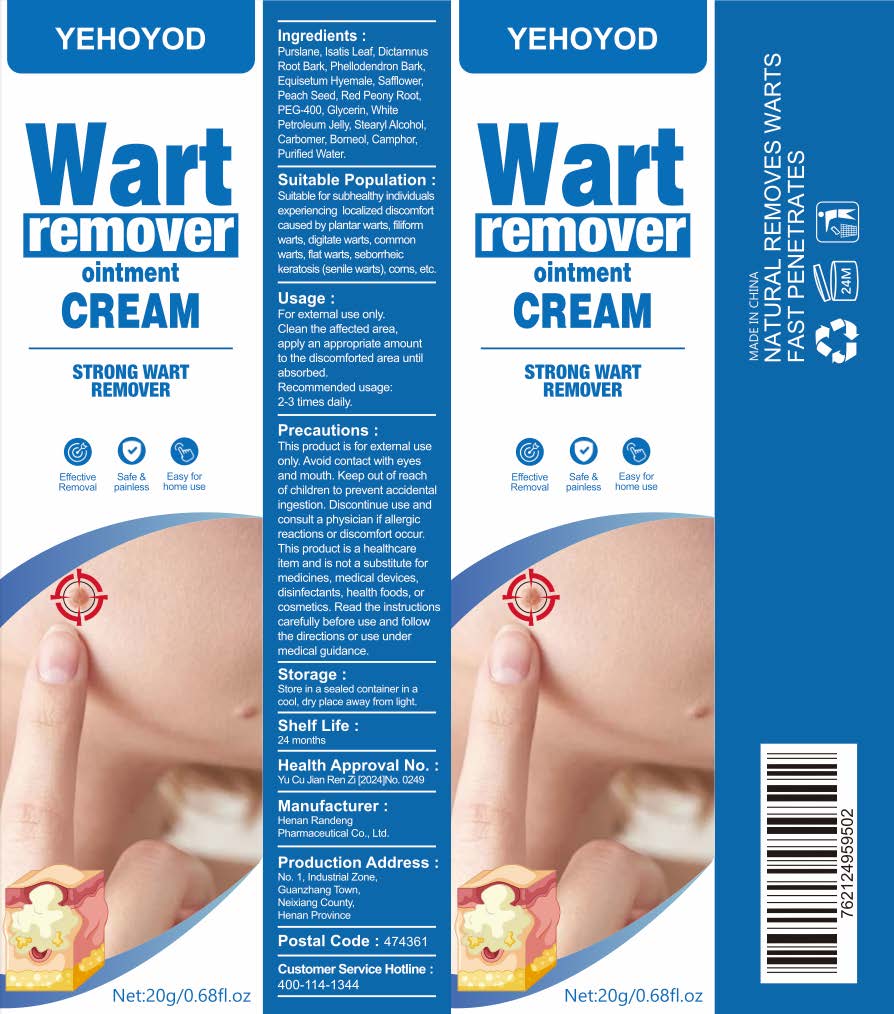 DRUG LABEL: Wart Remover
NDC: 84288-006 | Form: CREAM
Manufacturer: Dongkou County Hecheng Network Technology Co., Ltd.
Category: otc | Type: HUMAN OTC DRUG LABEL
Date: 20250717

ACTIVE INGREDIENTS: PHELLODENDRON AMURENSE BARK 0.2 g/100 g; PURSLANE 0.3 g/100 g
INACTIVE INGREDIENTS: PEG-400; CARBOMER; STEARYL ALCOHOL; GLYCERIN; BORNEOL

84288-006 YEHOYOD Wart remover ointment CREAM

ACTIVE INGREDIENT

Purslane
Phellodendron Bark

PURPOSE

STRONG WART REMOVER

INDICATIONS AND USAGE

Suitable for subnealthy indnviduaisexperiencing localized discomfortcaused by plantar warts, fformwaris, digilate warts, commonwarts, fat warts, seborheickeratosis (senile warts). cors. elo

WARNINGS

For external use only

WHEN USING

This product is for external useonly. Avoid contact with eyesand mouth. Keep out of reachof children to prevent accidentalingestion, Discontinle use andconsult a physician if allergicreactions or discomfort occur.This product is a healthcareitem and is not a subsiitute formedicines,medical devicesdisinfectants, health foods, orcosmetics.Read the instructionscarefully before use and followthe directions or use undermedical guidance

Keep out of reachof children to prevent accidentalingestion

DOSAGE AND ADMINISTRATION

Clean the affecled area.apply an approprate amountto the discomforted area untilabsorbed.Recommended usage.2-3 times daily.

INACTIVE INGREDIENT

PEG-400
Glycerin
Stearyl Alcohol
Carbomer
BORNEOL